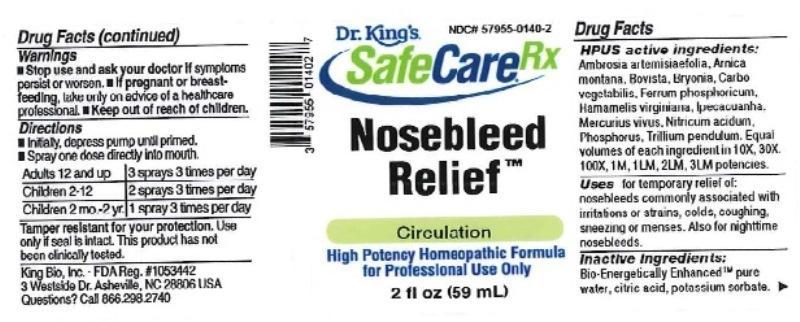 DRUG LABEL: Nosebleed Relief
NDC: 57955-0140 | Form: LIQUID
Manufacturer: King Bio Inc.
Category: homeopathic | Type: HUMAN OTC DRUG LABEL
Date: 20170320

ACTIVE INGREDIENTS: AMBROSIA ARTEMISIIFOLIA 10 [hp_X]/59 mL; ARNICA MONTANA 10 [hp_X]/59 mL; LYCOPERDON UTRIFORME FRUITING BODY 10 [hp_X]/59 mL; BRYONIA ALBA ROOT 10 [hp_X]/59 mL; ACTIVATED CHARCOAL 10 [hp_X]/59 mL; FERROSOFERRIC PHOSPHATE 10 [hp_X]/59 mL; HAMAMELIS VIRGINIANA ROOT BARK/STEM BARK 10 [hp_X]/59 mL; IPECAC 10 [hp_X]/59 mL; MERCURY 10 [hp_X]/59 mL; NITRIC ACID 10 [hp_X]/59 mL; PHOSPHORUS 10 [hp_X]/59 mL; TRILLIUM ERECTUM ROOT 10 [hp_X]/59 mL
INACTIVE INGREDIENTS: WATER; ANHYDROUS CITRIC ACID; POTASSIUM SORBATE

Nosebleed Relief™

ACTIVE INGREDIENT

Drug Facts__________________________________________________________________________________________________________

HPUS Active Ingredients: Ambrosia Artemisiaefolia, Arnica montana, Bovista, Bryonia, Carbo vegetabilis, Ferrum phosporicum, Hamamelis virginian, Ipecacuanha, Mercurius vivus, Nitricum acidum, Phosphorus, Trillium pendulum. Equal volumes of each ingredient in 10X, 30X, 100X, 1M, 1LM, 2LM, 3LM potencies.

INDICATIONS AND USAGE

Uses for temporary relief of nosebleeds commonly associated with irritations or strains, colds, coughing, sneezing or menses. Also for nightime nosebleeds.

Inactive Ingredients:

Bio-Energetically Enhanced™ pure water, citric acid and potassium sorbate.

Warnings

- Stop use and ask your doctor if symptoms persist or worsen.
- If pregnant or breast-feeding, take only on advice of a healthcare professional.

- Keep out of reach of children.

Directions

- Initially, depress pump until primed.
- Spray one dose directly into mouth.
- Adults 12 and up: 3 sprays 3 times per day.
- Children 2-12: 2 sprays 3 times per day.
- Children 2 mo-2yr: 1 spray 3 times per day.

OTHER SAFETY INFORMATION

Tamper resistant for your protection. Use only if safety seal is intact. This product has not been clinically tested.

PURPOSE

Uses for temporary relief of:

- nosebleeds commonly associated with irritations or strains
- colds
- coughing
- sneezing or menses
- nightime nosebleeds